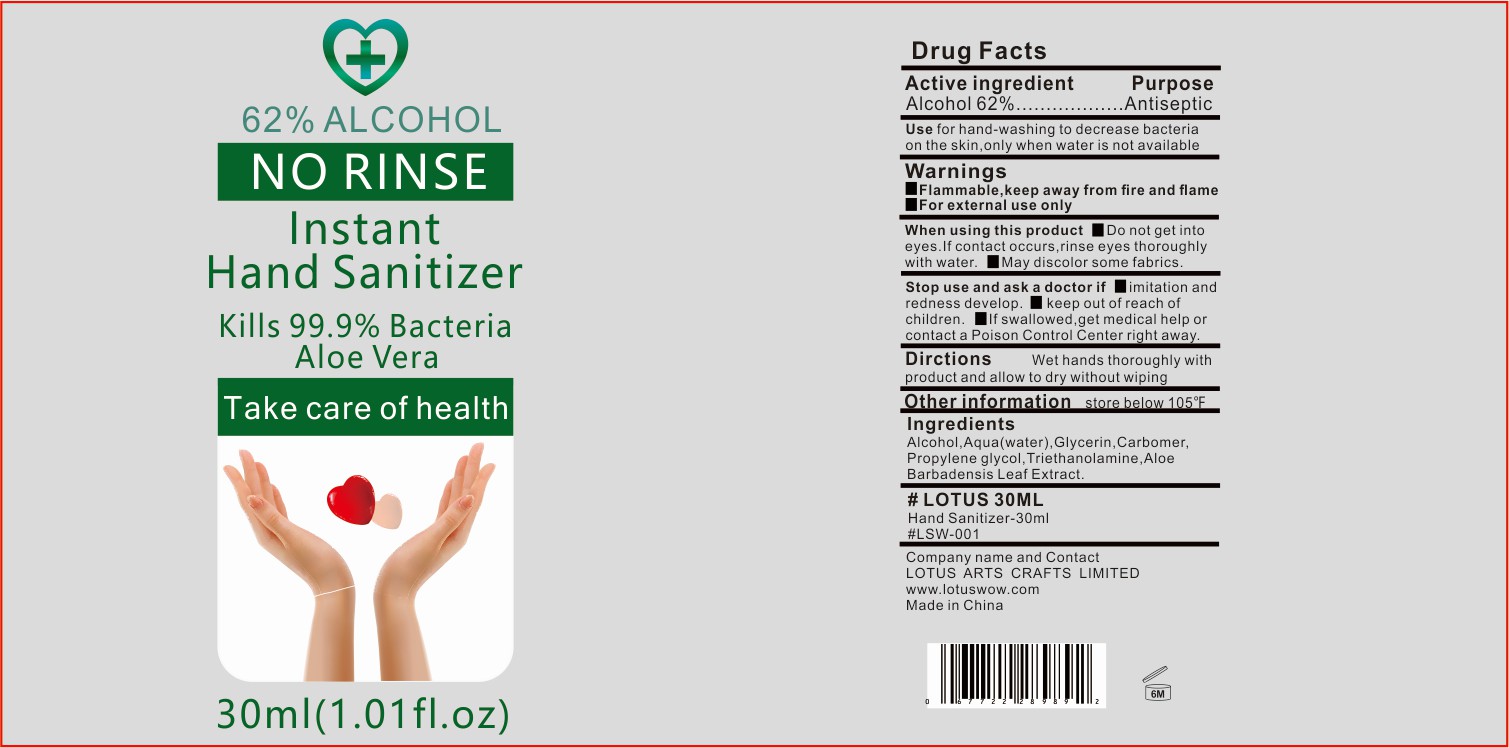 DRUG LABEL: Hand Sanitizer
NDC: 78294-002 | Form: GEL
Manufacturer: LOTUS ARTS CRAFTS LIMITED
Category: otc | Type: HUMAN OTC DRUG LABEL
Date: 20200822

ACTIVE INGREDIENTS: ALCOHOL 62 mL/100 mL
INACTIVE INGREDIENTS: WATER 36.6 mL/100 mL; TROLAMINE 0.3 mL/100 mL; GLYCERIN 0.5 mL/100 mL; ALOE VERA LEAF 0.1 mL/100 mL; CARBOMER 940 0.3 mL/100 mL; PROPYLENE GLYCOL 0.2 mL/100 mL

HAND SANITIZER